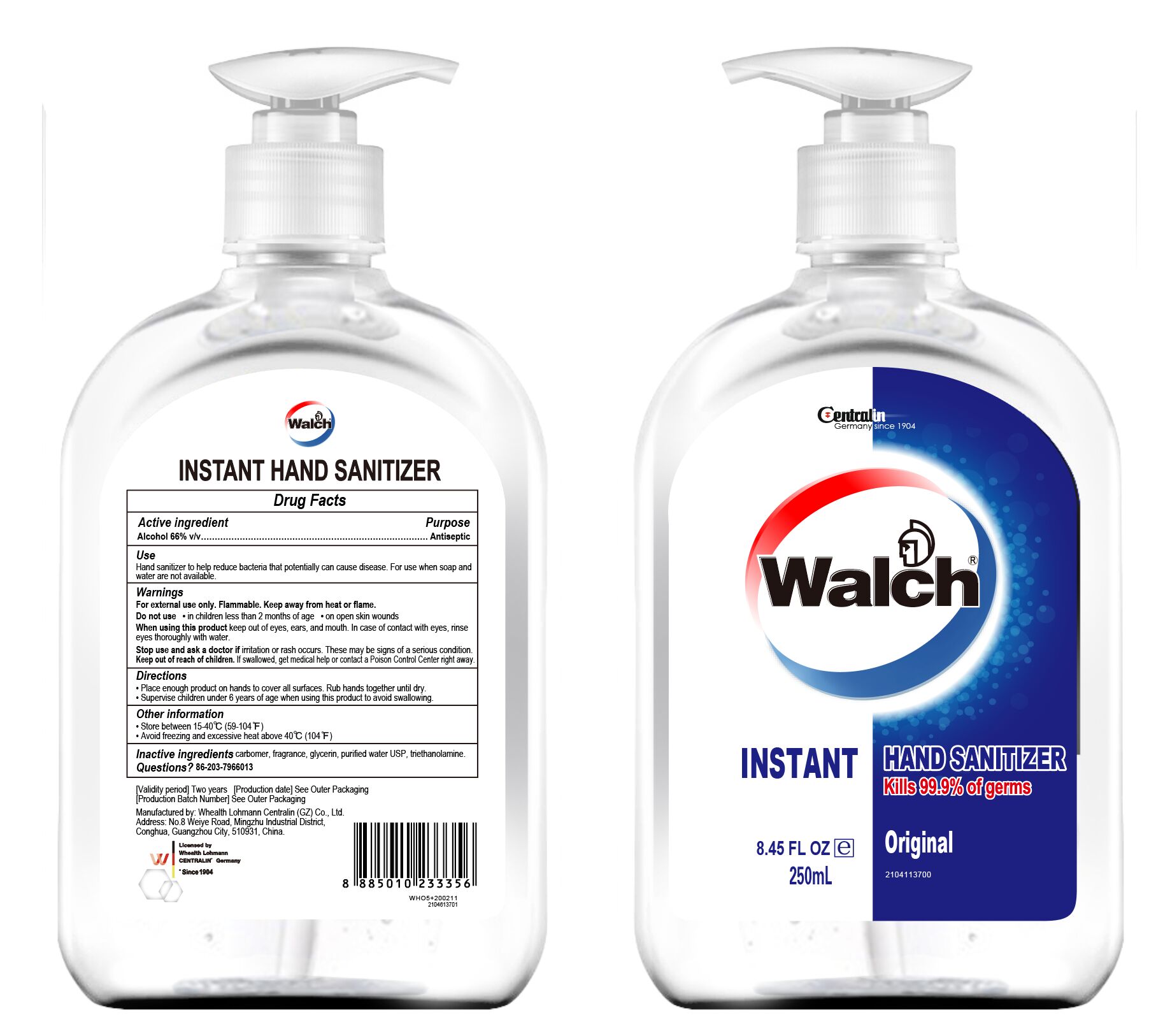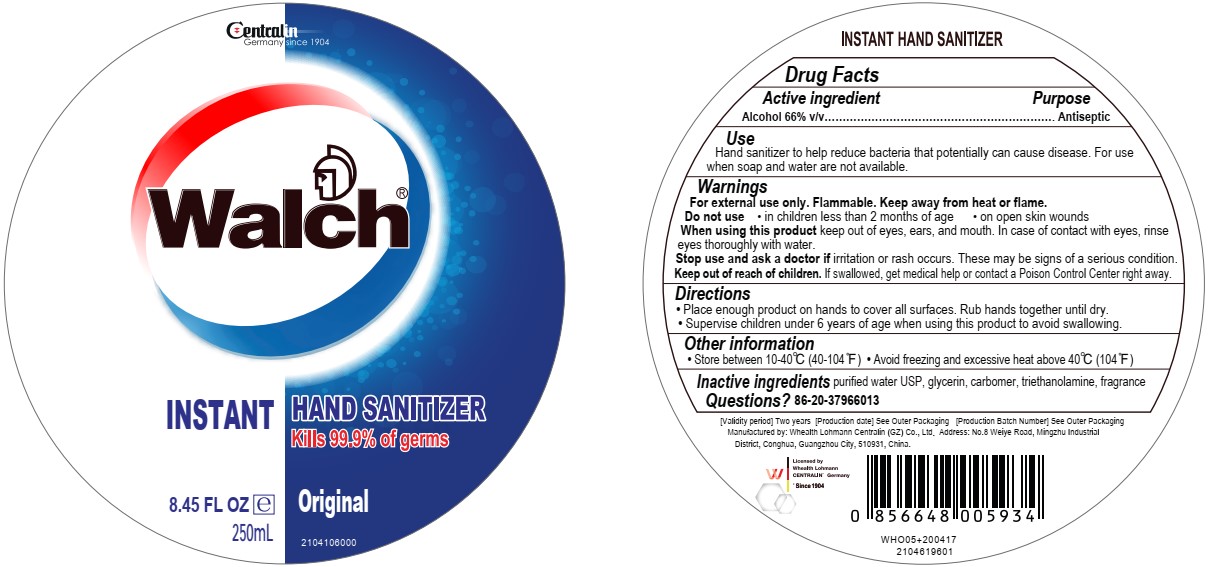 DRUG LABEL: INSTANT HAND SANITIZER
NDC: 77976-001 | Form: GEL
Manufacturer: Whealth Lohmann Centralin (GZ) Co., Ltd.
Category: otc | Type: HUMAN OTC DRUG LABEL
Date: 20200710

ACTIVE INGREDIENTS: ALCOHOL 165 mL/250 mL
INACTIVE INGREDIENTS: TROLAMINE 0.425 mL/250 mL; GLYCERIN 2.5 mL/250 mL; CARBOMER HOMOPOLYMER TYPE B (ALLYL SUCROSE CROSSLINKED) 0.625 mL/250 mL; WATER 81.4 mL/250 mL; FRAGRANCE LAVENDER & CHIA F-153480 0.05 mL/250 mL

Active Ingredient(s)

Alcohol 66% v/v. Purpose: Antiseptic

Purpose

Antiseptic, Hand Sanitizer

Use

Hand Sanitizer to help reduce bacteria that potentially can cause disease. For use when soap and water are not available.

Warnings

For external use only. Flammable. Keep away from heat or flame

Do not use

- in children less than 2 months of age
- on open skin wounds

When using this product keep out of eyes, ears, and mouth. In case of contact with eyes, rinse eyes thoroughly with water.
Stop use and ask a doctor if irritation or rash occurs. These may be signs of a serious condition.
Keep out of reach of children. If swallowed, get medical help or contact a Poison Control Center right away.

Stop use and ask a doctor if irritation or rash occurs. These may be signs of a serious condition.

Keep out of reach of children. If swallowed, get medical help or contact a Poison Control Center right away.

Directions

- Place enough product on hands to cover all surfaces. Rub hands together until dry.
- Supervise children under 6 years of age when using this product to avoid swallowing.

Other information

- Store between 15-40C (59-104F)
- Avoid freezing and excessive heat above 40C (104F)

Inactive ingredients

carbomer, fragrance, glycerin, purified water USP, triethanolamine.

Package Label - Principal Display Panel

250 mL NDC: 77976-001-92